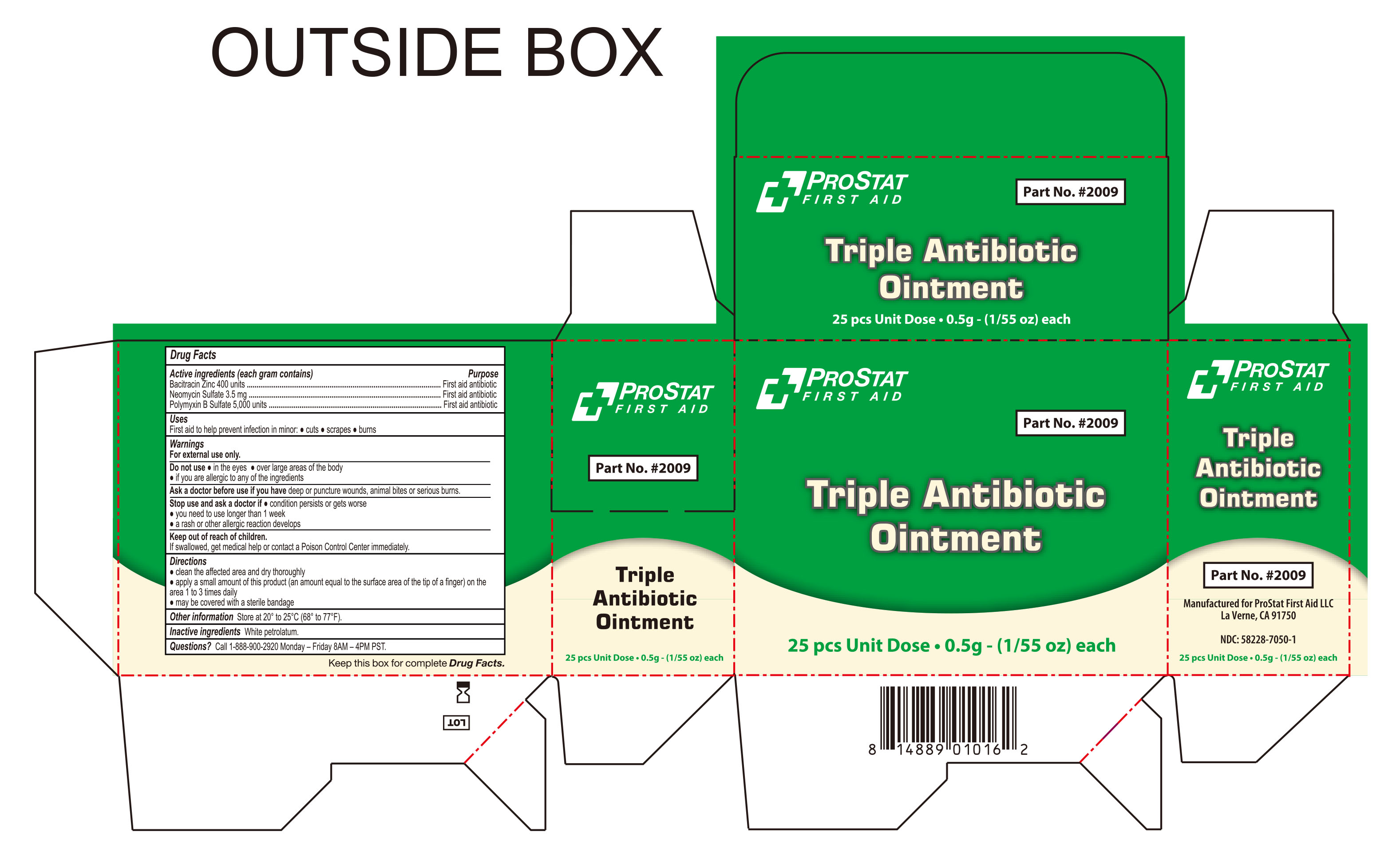 DRUG LABEL: Triple Antibiotic
NDC: 58228-7050 | Form: OINTMENT
Manufacturer: ProStat First Aid, LLC.
Category: otc | Type: HUMAN OTC DRUG LABEL
Date: 20260127

ACTIVE INGREDIENTS: BACITRACIN ZINC 400 [USP'U]/1 g; NEOMYCIN SULFATE 3.5 mg/1 g; POLYMYXIN B SULFATE 5000 [USP'U]/1 g
INACTIVE INGREDIENTS: WHITE PETROLATUM

Prostat First Aid Triple Antibiotic Ointment

Active ingredients (each gram contains)

Bacitracin zinc 400 units
Neomycin sulfate 3.5 mg
Polymyxin B sulfate 5,000 units

Purpose

First aid antibiotic

Keep out of reach of children. If swallowed, get medical help or contact a Poison Control Center immediately.

INDICATIONS AND USAGE

Uses first aid to help prevent infection in minor:● cuts ● scrapes ● burns

Warnings For external use only.

Do Not Use

- In the eyes
- over large areas of the body
- if you are allergic to any of the ingredients.

Directions

● clean the affected area and dry thoroughly.

● apply a small amount of this product (an amount equal to the surface area of the tip of a finger) on the area 1 to 3 times daily

● may be covered with a sterile bandage.

Inactive ingredientWhite Petrolatum

Ask a doctor before use if you have

Deep or puncture wounds, animal bites or serious burns.

Stop Use and Ask a doctor if

- Conditions persist or get worse
- you need to use longer than 1 week
- a rash or other allergic reaction develops

Other information

● store at 20° to 25°C (68° to 77°F)

Questions? Call 1-888-900-2920

Monday - Friday 8AM - 4PM PST

Manufactured for

ProStat First Aid LLC

La Verne, CA 91750

Part no. #2009